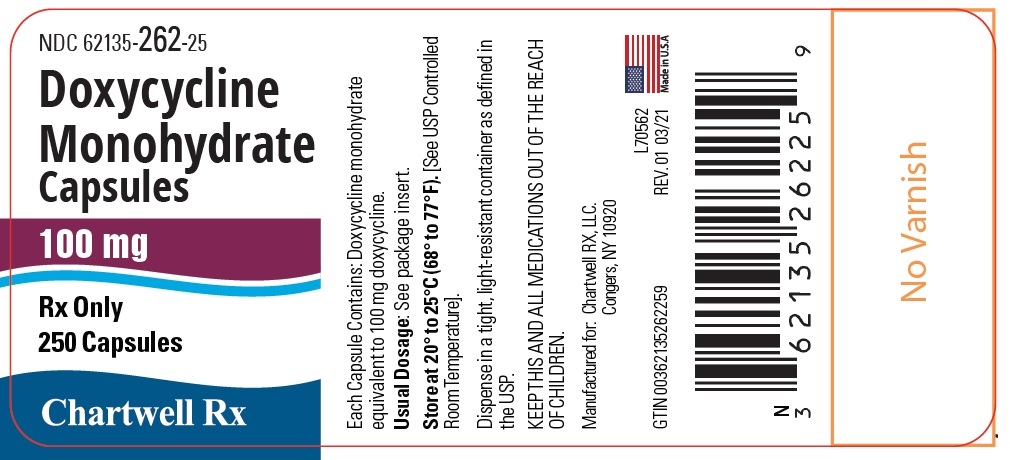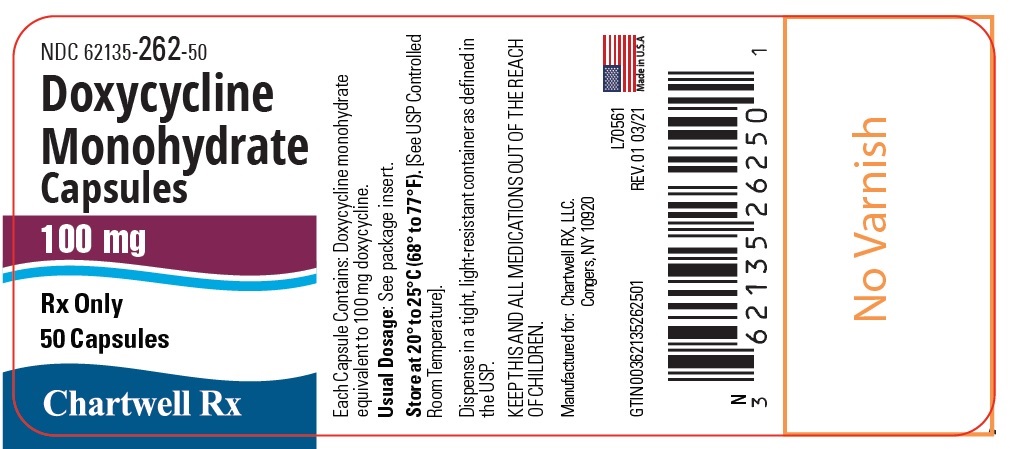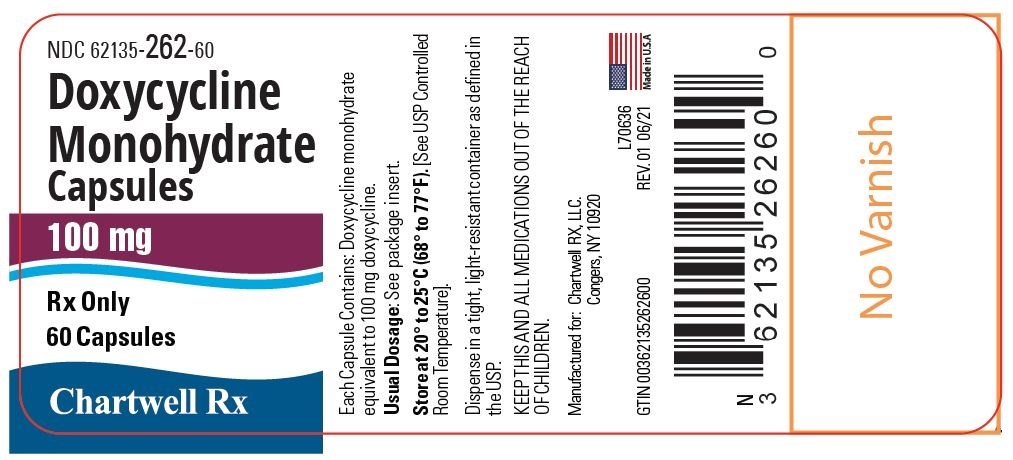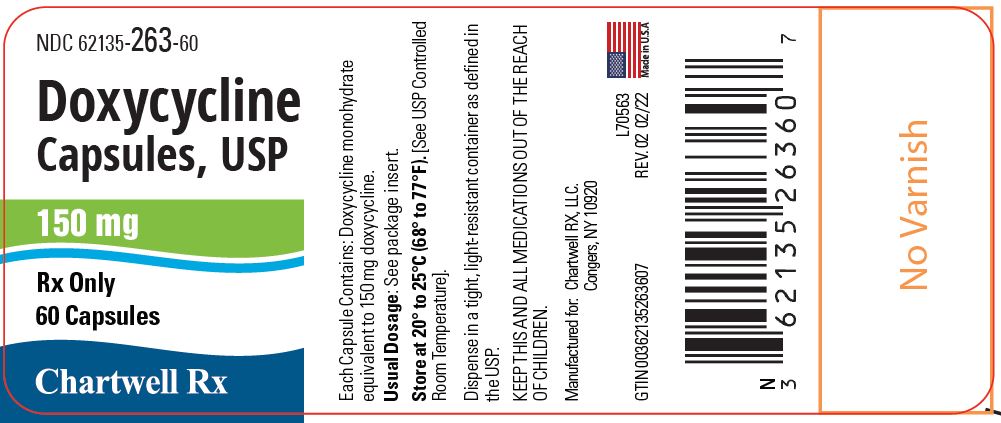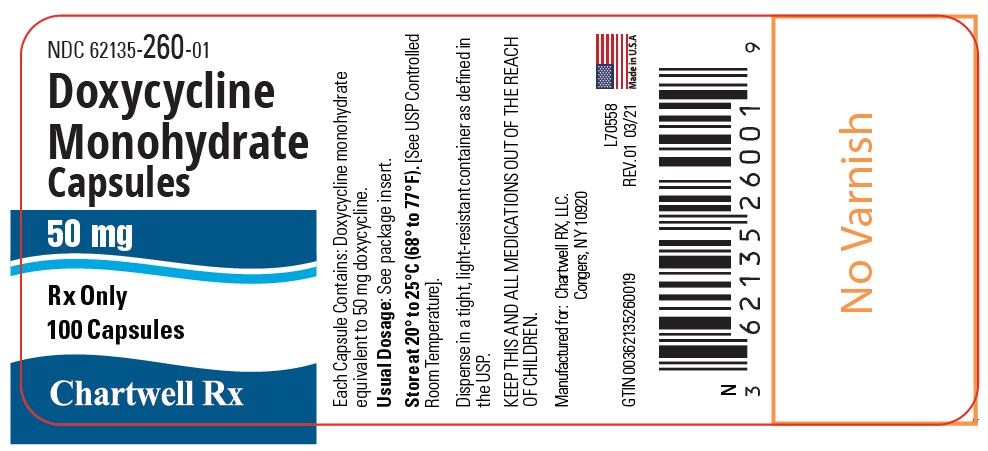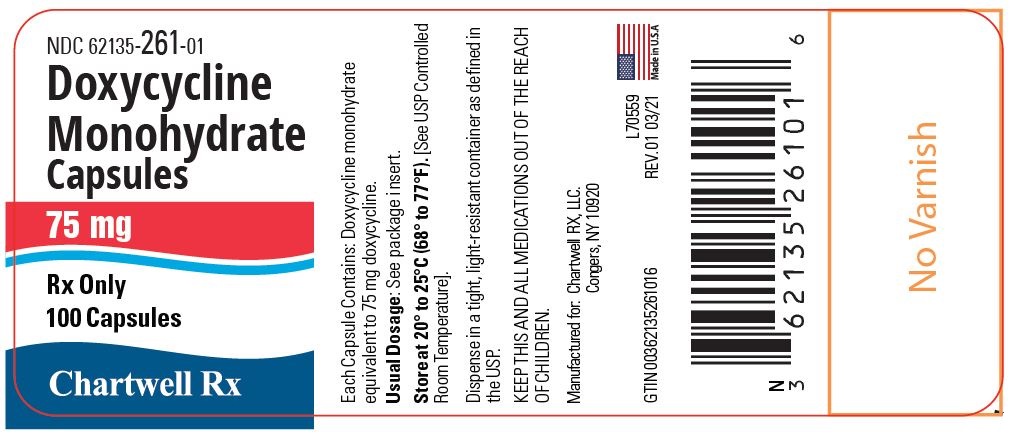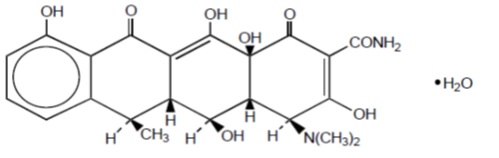 DRUG LABEL: Doxycycline Monohydrate
NDC: 62135-260 | Form: CAPSULE
Manufacturer: Chartwell RX, LLC.
Category: prescription | Type: HUMAN PRESCRIPTION DRUG LABEL
Date: 20250725

ACTIVE INGREDIENTS: DOXYCYCLINE 50 mg/1 1
INACTIVE INGREDIENTS: SILICON DIOXIDE; MAGNESIUM STEARATE; MICROCRYSTALLINE CELLULOSE; SODIUM STARCH GLYCOLATE TYPE A POTATO; FERROSOFERRIC OXIDE; TITANIUM DIOXIDE; FERRIC OXIDE YELLOW; D&C YELLOW NO. 10; FD&C BLUE NO. 1; FD&C RED NO. 40; FD&C BLUE NO. 2

Doxycycline Capsules, USP

Doxycycline Capsules, USP

Rx only

To reduce the development of drug-resistant bacteria and maintain the effectiveness of doxycycline capsules and other antibacterial drugs, doxycycline capsules should be used only to treat or prevent infections that are proven or strongly suspected to be caused by bacteria.

DESCRIPTION

Doxycycline is a broad-spectrum antibacterial synthetically derived from oxytetracycline. Doxycycline capsules 150 mg, 100 mg, 75 mg, and 50 mg contain doxycycline monohydrate equivalent to 150 mg, 100 mg, 75 mg, or 50 mg of doxycycline for oral administration. The chemical designation of the light-yellow crystalline powder is alpha-6-deoxy-5-oxytetracycline.

Structural formula:

C22H24N2O8• H2O M.W. = 462.45

Doxycycline has a high degree of lipid solubility and a low affinity for calcium binding. It is highly stable in normal human serum. Doxycycline will not degrade into an epianhydro form.

Inert ingredients: colloidal silicon dioxide; magnesium stearate; microcrystalline cellulose; sodium starch glycolate; and a hard gelatin capsule which contains black iron oxide, red iron oxide, titanium dioxide, and yellow iron oxide for the 150 mg, 100 mg and 75 mg strengths, titanium dioxide and yellow iron oxide for the 50 mg strength. The capsules are printed with edible ink containing black iron oxide, FD&C Blue No. 2, FD&C Red No. 40, FD&C Blue No. 1, and D&C Yellow No. 10.

CLINICAL PHARMACOLOGY

Tetracyclines are readily absorbed and are bound to plasma proteins in varying degrees. They are concentrated by the liver in the bile and excreted in the urine and feces at high concentrations in a biologically active form. Doxycycline is virtually completely absorbed after oral administration.

Following a 200 mg dose of doxycycline monohydrate, 24 normal adult volunteers averaged the following serum concentration values:

Time (hr): 0.5 | 1.0 | 1.5 | 2.0 | 3.0 | 4.0 | 8.0 | 12.0 | 24.0 | 48.0 | 72.0
Conc. 1.02 | 2.26 | 2.67 | 3.01 | 3.16 | 3.03 | 2.03 | 1.62 | 0.95 | 0.37 | 0.15 (μg/mL)

Average Observed Values

Maximum Concentration 3.61 μg/mL (± 0.9 sd)
Time of Maximum Concentration 2.60 hr (± 1.10 sd)
Elimination Rate Constant 0.049 per hr (± 0.030 sd)
Half-Life 16.33 hr (± 4.53 sd)

Excretion of doxycycline by the kidney is about 40%/72 hours in individuals with normal function (creatinine clearance about 75 mL/min). This percentage excretion may fall as low as 1-5%/72 hours in individuals with severe renal insufficiency (creatinine clearance below 10 mL/min). Studies have shown no significant difference in serum half-life of doxycycline (range 18-22 hours) in individuals with normal and severely impaired renal function.

Hemodialysis does not alter serum half-life.

Results of animal studies indicate that tetracyclines cross the placenta and are found in fetal tissues.

Population pharmacokinetic analysis of sparse concentration-time data of doxycycline following standard of care intravenous and oral dosing in 44 pediatric patients (2-18 years of age) showed that allometrically-scaled clearance (CL) of doxycycline in pediatric patients ≥2 to ≤8 years of age (median [range] 3.58 [2.27-10.82] L/h/70 kg, N=11) did not differ significantly from pediatric patients >8 to 18 years of age (3.27 [1.11-8.12] L/h/70 kg, N=33). For pediatric patients weighing ≤45 kg, body weight normalized doxycycline CL in those ≥2 to ≤8 years of age (median [range] 0.071 [0.041-0.202] L/kg/h, N=10) did not differ significantly from those >8 to 18 years of age (0.081 [0.035-0.126] L/kg/h, N=8). In pediatric patients weighing >45 kg, no clinically significant differences in body weight normalized doxycycline CL were observed between those ≥2 to ≤8 years (0.050 L/kg/h, N=1) and those >8 to 18 years of age (0.044 [0.014-0.121] L/kg/h, N=25). No clinically significant difference in CL between oral and IV dosing was observed in the small cohort of pediatric patients who received the oral (N=19) or IV (N=21) formulation alone.

Microbiology:

Mechanism of Action

Doxycycline inhibits bacterial protein synthesis by binding to the 30S ribosomal subunit. Doxycycline has bacteriostatic activity against a broad range of Gram-positive and Gram-negative bacteria.

Resistance

Cross resistance with other tetracyclines is common.

Antimicrobial Activity

Doxycycline has been shown to be active against most isolates of the following microorganisms, both in vitroand in clinical infections (see INDICATIONS AND USAGE) .

Gram-negative Bacteria

Acinetobacterspecies
Bartonella bacilliformis
Brucellaspecies
Campylobacter fetus
Enterobacter aerogenes
Escherichia coli
Francisella tularensis
Haemophilus ducreyi
Haemophilus influenzae
Klebsiella granulomatis
Klebsiellaspecies
Neisseria gonorrhoeae
Shigellaspecies
Vibrio cholerae
Yersinia pestis

Gram-positive Bacteria

Bacillus anthracis
Listeria monocytogenes
Streptococcus pneumoniae

Anaerobic Bacteria

Clostridiumspecies
Fusobacterium fusiforme
Propionibacterium acnes

Other Bacteria

Nocardiaeand other Actinomycesspecies
Borrelia recurrentis
Chlamydophila psittaci
Chlamydia trachomatis
Mycoplasma pneumoniae
Rickettsiae
Treponema pallidum
Treponema pallidumsubspecies pertenue
Ureaplasma urealyticum

Parasites

Balantidium coli
Entamoebaspecies

Susceptibility Testing

For specific information regarding susceptibility test interpretive criteria, and associated test methods and quality control standards recognized by FDA for this drug, please see: http://www.fda.gov/STIC.

INDICATIONS AND USAGE

To reduce the development of drug-resistant bacteria and maintain effectiveness of doxycycline capsules and other antibacterial drugs, doxycycline capsules should be used only to treat or prevent infections that are proven or strongly suspected to be caused by susceptible bacteria. When culture and susceptibility information are available, they should be considered in selecting or modifying antibacterial therapy. In the absence of such data, local epidemiology and susceptibility patterns may contribute to the empiric selection of therapy.

Doxycycline is indicated for the treatment of the following infections:

Rocky mountain spotted fever, typhus fever and the typhus group, Q fever, rickettsialpox, and tick fevers caused by Rickettsiae.
Respiratory tract infections caused by Mycoplasma pneumoniae.
Lymphogranuloma venereum caused by Chlamydia trachomatis.
Psittacosis (ornithosis) caused by Chlamydophila psittaci.
Trachoma caused by Chlamydia trachomatis,although the infectious agent is not always eliminated as judged by immunofluorescence.
Inclusion conjunctivitis caused by Chlamydia trachomatis.
Uncomplicated urethral, endocervical or rectal infections in adults caused by Chlamydia trachomatis.
Nongonococcal urethritis caused by Ureaplasma urealyticum.
Relapsing fever due to Borrelia recurrentis.

Doxycycline is also indicated for the treatment of infections caused by the following gram-negative microorganisms:

Chancroid caused by Haemophilus ducreyi.
Plague due to Yersinia pestis.
Tularemia due to Francisella tularensis.
Cholera caused by Vibrio cholerae.
Campylobacter fetus infections caused by Campylobacter fetus.
Brucellosis due to Brucella species(in conjunction with streptomycin).
Bartonellosis due to Bartonella bacilliformis.
Granuloma inguinale caused by Klebsiella granulomatis.

Because many strains of the following groups of microorganisms have been shown to be resistant to doxycycline, culture and susceptibility testing are recommended.

Doxycycline is indicated for treatment of infections caused by the following gram-negative microorganisms, when bacteriologic testing indicates appropriate susceptibility to the drug:

Escherichia coli
Enterobacter aerogenes
Shigella species
Acinetobacter species
Respiratory tract infections caused by Haemophilus influenzae.
Respiratory tract and urinary tract infections caused by Klebsiella species.

Doxycycline is indicated for treatment of infections caused by the following gram-positive microorganisms when bacteriologic testing indicates appropriate susceptibility to the drug:

Upper respiratory infections caused by Streptococcus pneumoniae.
Anthrax due to Bacillus anthracis,including inhalational anthrax (post-exposure): to reduce the incidence or progression of disease following exposure to aerosolized Bacillus anthracis.

When penicillin is contraindicated, doxycycline is an alternative drug in the treatment of the following infections:

Uncomplicated gonorrhea caused by Neisseria gonorrhoeae.
Syphilis caused by Treponema pallidum.
Yaws caused by Treponema pallidumsubspecies pertenue.
Listeriosis due to Listeria monocytogenes.
Vincent’s infection caused by Fusobacterium fusiforme.
Actinomycosis caused by Actinomyces israelii.
Infections caused by Clostridiumspecies.

In acute intestinal amebiasis, doxycycline may be a useful adjunct to amebicides.

In severe acne, doxycycline may be useful adjunctive therapy.

CONTRAINDICATIONS

This drug is contraindicated in persons who have shown hypersensitivity to any of the tetracyclines.

WARNINGS

The use of drugs of the tetracycline class, including doxycycline, during tooth development (last half of pregnancy, infancy and childhood to the age of 8 years) may cause permanent discoloration of the teeth (yellow-gray-brown). This adverse reaction is more common during long-term use of the drugs, but it has been observed following repeated short-term courses. Enamel hypoplasia has also been reported. Use of doxycycline in pediatric patients 8 years of age or less only when the potential benefits are expected to outweigh the risks in severe or life-threatening conditions (e.g. anthrax, Rocky Mountain spotted fever), particularly when there are no alternative therapies.

Clostridium difficileassociated diarrhea (CDAD) has been reported with use of nearly all antibacterial agents, including doxycycline capsules, and may range in severity from mild diarrhea to fatal colitis. Treatment with antibacterial agents alters the normal flora of the colon leading to overgrowth of C. difficile.

C. difficileproduces toxins A and B which contribute to the development of CDAD. Hypertoxin producing strains of C. difficilecause increased morbidity and mortality, as these infections can be refractory to antimicrobial therapy and may require colectomy. CDAD must be considered in all patients who present with diarrhea following antibiotic use. Careful medical history is necessary since CDAD has been reported to occur over two months after the administration of antibacterial agents.

If CDAD is suspected or confirmed, ongoing antibiotic use not directed against C. difficilemay need to be discontinued. Appropriate fluid and electrolyte management, protein supplementation, antibiotic treatment of C. difficile, and surgical evaluation should be instituted as clinically indicated.

Intracranial hypertension (IH, pseudotumor cerebri) has been associated with the use of tetracyclines including doxycycline capsules. Clinical manifestations of IH include headache, blurred vision, diplopia, and vision loss; papilledema can be found on fundoscopy. Women of childbearing age who are overweight or have a history of IH are at greater risk for developing tetracycline associated IH. Concomitant use of isotretinoin and doxycycline capsules should be avoided because isotretinoin is also known to cause pseudotumor cerebri.

Although IH typically resolves after discontinuation of treatment, the possibility for permanent visual loss exists. If visual disturbance occurs during treatment, prompt ophthalmologic evaluation is warranted. Since intracranial pressure can remain elevated for weeks after drug cessation patients should be monitored until they stabilize.

All tetracyclines form a stable calcium complex in any bone-forming tissue. A decrease in the fibula growth rate has been observed in prematures given oral tetracycline in doses of 25 mg/kg every six hours. This reaction was shown to be reversible when the drug was discontinued.

Results of animal studies indicate that tetracyclines cross the placenta, are found in fetal tissues, and can have toxic effects on the developing fetus (often related to retardation of skeletal development). Evidence of embryo toxicity has been noted in animals treated early in pregnancy. If any tetracycline is used during pregnancy or if the patient becomes pregnant while taking these drugs, the patient should be apprised of the potential hazard to the fetus.

The antianabolic action of the tetracyclines may cause an increase in BUN. Studies to date indicate that this does not occur with the use of doxycycline in patients with impaired renal function.

Photosensitivity manifested by an exaggerated sunburn reaction has been observed in some individuals taking tetracyclines. Patients apt to be exposed to direct sunlight or ultraviolet light should be advised that this reaction can occur with tetracycline drugs, and treatment should be discontinued at the first evidence of skin erythema.

Fixed drug eruptions have occurred with doxycycline and have been associated with worsening severity upon subsequent administrations, including generalized bullous fixed drug eruption (see ADVERSE REACTIONS). If severe skin reactions occur, discontinue doxycycline capsules immediately and institute appropriate therapy.

PRECAUTIONS

General:

As with other antibacterial preparations, use of this drug may result in overgrowth of non-susceptible organisms, including fungi. If superinfection occurs, doxycycline capsules should be discontinued and appropriate therapy instituted.

Incision and drainage or other surgical procedures should be performed in conjunction with antibacterial therapy when indicated.

Prescribing doxycycline capsules in the absence of proven or strongly suspected bacterial infection or a prophylactic indication is unlikely to provide benefit to the patient and increases the risk of the development of drug-resistant bacteria.

Information for Patients:

All patients taking doxycycline should be advised:

–to avoid excessive sunlight or artificial ultraviolet light while receiving doxycycline and to discontinue therapy if phototoxicity (e.g., skin eruptions, etc.) occurs. Sunscreen or sunblock should be considered (see WARNINGS).

–to drink fluids liberally along with doxycycline to reduce the risk of esophageal irritation and ulceration (see ADVERSE REACTIONS).

–that the absorption of tetracyclines is reduced when taken with foods, especially those which contain calcium. However, the absorption of doxycycline is not markedly influenced by simultaneous ingestion of food or milk (see Drug Interactions).

–that the absorption of tetracyclines is reduced when taking bismuth subsalicylate (see Drug Interactions).

–not to use outdated or poorly stored doxycycline.

–that the use of doxycycline might increase the incidence of vaginal candidiasis.

Diarrhea is a common problem caused by antibiotics which usually ends when the antibiotic is discontinued. Sometimes after starting treatment with antibiotics, patients can develop watery and bloody stools (with or without stomach cramps and fever) even as late as two or more months after having taken the last dose of the antibiotic. If this occurs, patients should contact their physician as soon as possible.

Patients should be counseled that antibacterial drugs including doxycycline capsules should only be used to treat bacterial infections. They do not treat viral infections (e.g., the common cold). When doxycycline capsules are prescribed to treat a bacterial infection, patients should be told that although it is common to feel better early in the course of therapy, the medication should be taken exactly as directed. Skipping doses or not completing the full course of therapy may (1) decrease the effectiveness of the immediate treatment and (2) increase the likelihood that bacteria will develop resistance and will not be treatable by doxycycline capsules or other antibacterial drugs in the future.

Laboratory Tests:

In venereal disease when coexistent syphilis is suspected, a dark-field examination should be done before treatment is started and the blood serology repeated monthly for at least four months.

In long-term therapy, periodic laboratory evaluations of organ systems, including hematopoietic, renal, and hepatic studies should be performed.

Drug Interactions:

Because tetracyclines have been shown to depress plasma prothrombin activity, patients who are on anticoagulant therapy may require downward adjustment of their anticoagulant dosage.

Since bacteriostatic drugs may interfere with the bactericidal action of penicillin, it is advisable to avoid giving tetracyclines in conjunction with penicillin.

Absorption of tetracyclines is impaired by antacids containing aluminum, calcium, or magnesium, and iron-containing preparations.

Absorption of tetracyclines is impaired by bismuth subsalicylate.

Barbiturates, carbamazepine, and phenytoin decrease the half-life of doxycycline.

Concurrent use of tetracycline may render oral contraceptives less effective.

Drug/Laboratory Test Interactions:

False elevations of urinary catecholamine levels may occur due to interference with the fluorescence test.

Carcinogenesis, Mutagenesis, Impairment of Fertility:

Long-term studies in animals to evaluate the carcinogenic potential of doxycycline have not been conducted. However, there has been evidence of oncogenic activity in rats in studies with related antibacterial, oxytetracycline (adrenal and pituitary tumors) and minocycline (thyroid tumors). Likewise, although mutagenicity studies of doxycycline have not been conducted, positive results in in vitromammalian cell assays have been reported for related antibacterial (tetracycline, oxytetracycline). Doxycycline administered orally at dosage levels as high as 250 mg/kg/day had no apparent effect on the fertility of female rats. Effect on male fertility has not been studied.

Pregnancy:

Teratogenic Effects.

Pregnancy Category D:

There are no adequate and well-controlled studies on the use of doxycycline in pregnant short-term, first trimester exposure. There are no human data available to assess the effects of long-term therapy of doxycycline in pregnant women such as that proposed for treatment of anthrax exposure. An expert review of published data on experiences with doxycycline use during pregnancy by TERIS - the Teratogen Information System - concluded that therapeutic doses during pregnancy are unlikely to pose a substantial teratogenic risk (the quantity and quality of data were assessed as limited to fair), but the data are insufficient to state that there is no risk.^1

A case-control study (18,515 mothers of infants with congenital anomalies and 32,804 mothers of infants with no congenital anomalies) shows a weak but marginally statistically significant association with total malformations and use of doxycycline anytime during pregnancy. (Sixty-three [0.19%] of the controls and 56 [0.30%] of the cases were treated with doxycycline.) This association was not seen when the analysis was confined to maternal treatment during the period of organogenesis (i.e., in the second and third months of gestation) with the exception of a marginal relationship with neural tube defect based on only two exposed cases.^2

A small prospective study of 81 pregnancies describes 43 pregnant women treated for 10 days with doxycycline during early first trimester. All mothers reported their exposed infants were normal at 1 year of age.^3

Labor and Delivery:

The effect of tetracyclines on labor and delivery is unknown.

Nursing Mothers:

Tetracyclines are excreted in human milk, however, the extent of absorption of tetracyclines, including doxycycline, by the breastfed infant is not known. Short-term use by lactating women is not necessarily contraindicated; however, the effects of prolonged exposure to doxycycline in breast milk are unknown.^4Because of the potential for adverse reactions in nursing infants from doxycycline, a decision should be made whether to discontinue nursing or to discontinue the drug, taking into account the importance of the drug to the mother (see WARNINGS).

Pediatric Use:

Because of the effects of drugs of the tetracycline –class, on tooth development and growth, use doxycycline in pediatric patients 8 years of age or less only when the potential benefits are expected to outweigh the risks in severe or life-threatening conditions (e.g. anthrax, Rocky Mountain spotted fever), particularly when there are no alternative therapies (see WARNINGSand DOSAGE AND ADMINISTRATION).

ADVERSE REACTIONS

Due to oral doxycycline’s virtually complete absorption, side effects to the lower bowel, particularly diarrhea, have been infrequent. The following adverse reactions have been observed in patients receiving tetracyclines.

Gastrointestinal:Anorexia, nausea, vomiting, diarrhea, glossitis, dysphagia, enterocolitis, and inflammatory lesions (with monilial overgrowth) in the anogenital region, and pancreatitis. Hepatotoxicity has been reported. These reactions have been caused by both the oral and parenteral administration of tetracyclines. Rare instances of esophagitis and esophageal ulcerations have been reported in patients receiving capsule and tablet forms of drugs in the tetracycline class. Most of these patients took medications immediately before going to bed (see DOSAGE AND ADMINISTRATION).

Skin:Maculopapular and erythematous rashes, Stevens-Johnson syndrome, toxic epidermal necrolysis, erythema multiforme, and fixed drug eruption have been reported. Exfoliative dermatitis has been reported but is uncommon. Photosensitivity is discussed above (see WARNINGS).

Renal Toxicity:Rise in BUN has been reported and is apparently dose related (see WARNINGS).

Hypersensitivity Reactions:Urticaria, angioneurotic edema, anaphylaxis, anaphylactoid purpura, serum sickness, pericarditis, and exacerbation of systemic lupus erythematosus.

Blood:Hemolytic anemia, thrombocytopenia, neutropenia, and eosinophilia have been reported with tetracyclines.

Psychiatric:Depression, anxiety, suicidal ideation, insomnia, abnormal dreams, hallucination

Other:Intracranial hypertension (IH, pseudotumor cerebri) has been associated with the use of tetracyclines (see PRECAUTIONS-General).

When given over prolonged periods, tetracyclines have been reported to produce brown-black microscopic discoloration of the thyroid gland. No abnormalities of thyroid function are known to occur.

OVERDOSAGE

In case of overdosage, discontinue medication, treat symptomatically and institute supportive measures. Dialysis does not alter serum half-life, and it would not be of benefit in treating cases of overdosage.

DOSAGE AND ADMINISTRATION

THE USUAL DOSAGE AND FREQUENCY OF ADMINISTRATION OF DOXYCYCLINE DIFFERS FROM THAT OF THE OTHER TETRACYCLINES. EXCEEDING THE RECOMMENDED DOSAGE MAY RESULT IN AN INCREASED INCIDENCE OF SIDE EFFECTS.

Adults:The usual dose of oral doxycycline is 200 mg on the first day of treatment (administered 100 mg every 12 hours or 50 mg every 6 hours) followed by a maintenance dose of 100 mg/day. The maintenance dose may be administered as a single dose or as 50 mg every 12 hours. In the management of more severe infections (particularly chronic infections of the urinary tract), 100 mg every 12 hours is recommended.

Pediatric Patients:

For all pediatric patients weighing less than 45 kg with severe or life-threatening infections (e.g. anthrax, Rocky Mountain spotted fever), the recommended dosage is 2.2 mg/kg of body weight administered every 12 hours. Children weighing 45 kg or more should receive the adult dose (see WARNINGSand PRECAUTIONS).

For pediatric patients with less severe disease (greater than 8 years of age and weighing less than 45 kg), the recommended dosage schedule is 4.4 mg per kg of body weight divided into two doses on the first day of treatment, followed by a maintenance dose of 2.2 mg per kg of body weight (given as a single daily dose or divided into twice daily doses). For pediatric patients weighing over 45 kg, the usual adult dose should be used.

The therapeutic antibacterial serum activity will usually persist for 24 hours following recommended dosage.

When used in streptococcal infections, therapy should be continued for 10 days.

Administration of adequate amounts of fluid along with capsule and tablet forms of drugs in the tetracycline class is recommended to wash down the drugs and reduce the risk of esophageal irritation and ulceration (see ADVERSE REACTIONS).

If gastric irritation occurs, it is recommended that doxycycline be given with food or milk. The absorption of doxycycline is not markedly influenced by simultaneous ingestion of food or milk.

Studies to date have indicated that administration of doxycycline at the usual recommended doses does not lead to excessive accumulation of doxycycline in patients with renal impairment.

Uncomplicated gonococcal infections in adults (except anorectal infections in men):100 mg, by mouth, twice a day for 7 days. As an alternate single visit dose, administer 300 mg stat followed in one hour by a second 300 mg dose.

Acute epididymo-orchitis caused by N. gonorrhoeae:100 mg, by mouth, twice a day for at least 10 days.

Primary and secondary syphilis:300 mg a day in divided doses for at least 10 days.

Uncomplicated urethral, endocervical, or rectal infection in adults caused by Chlamydia trachomatis:100 mg, by mouth, twice a day for at least 7 days.

Nongonococcal urethritis caused by C. trachomatisand U. urealyticum:100 mg, by mouth, twice a day for at least 7 days.

Acute epididymo-orchitis caused by C. trachomatis:100 mg, by mouth, twice a day for at least 10 days.

Inhalational anthrax (post-exposure):ADULTS: 100 mg of doxycycline, by mouth, twice a day for 60 days. CHILDREN: weighing less than 45 kg 2.2 mg/kg of body weight, by mouth, twice a day for 60 days. Children weighing 45 kg or more should receive the adult dose.

HOW SUPPLIED

Doxycycline capsules, USP 50 mg have a white opaque body with an ivory opaque cap imprinted with “CE” over “410” in black ink on cap and imprinted “50” over “mg” in black ink on body. Each capsule contains doxycycline monohydrate equivalent to 50 mg doxycycline.

Doxycycline capsules, USP 50 mg is available in:
Bottles of 100 capsules ......................................................NDC 62135-260-01

Doxycycline capsules, USP 75 mg have a white opaque body with a brown opaque cap imprinted with “CE” over “412” in white ink on cap and imprinted “75” over “mg” in black ink on body. Each capsule contains doxycycline monohydrate equivalent to 75 mg doxycycline.

Doxycycline capsules, USP 75 mg is available in:
Bottles of 100 capsules ......................................................NDC 62135-261-01

Doxycycline capsules, USP 100 mg have an ivory opaque body with a brown opaque cap imprinted with “CE” over “411” in white ink on cap and imprinted “100” over “mg” in black ink on body. Each capsule contains doxycycline monohydrate equivalent to 100 mg of doxycycline.

Doxycycline capsules, USP 100 mg is available in:
Bottles of 20 capsules ........................................................NDC 62135-262-20

Bottles of 50 capsules ........................................................NDC 62135-262-50

Bottles of 60 capsules ........................................................NDC 62135-262-60

Bottles of 250 capsules ......................................................NDC 62135-262-25

Doxycycline capsules, USP 150 mg have a brown opaque body with a brown opaque cap imprinted with “CE” over “413” in white ink on cap and imprinted “150” over “mg” in white ink on body. Each capsule contains doxycycline monohydrate equivalent to 150 mg doxycycline.

Doxycycline capsules, USP 150 mg is available in:
Bottles of 60 capsules ......................................................NDC 62135-263-60

STORE AT 20° to 25°C (68° to 77°F) WITH EXCURSIONS PERMITTED TO 15°C TO 30°C (59° TO 86°F). [SEE USP CONTROLLED ROOM TEMPERATURE.]

DISPENSE IN A TIGHT LIGHT-RESISTANT CONTAINER AS DEFINED IN THE USP/NF.

ANIMAL PHARMACOLOGY AND ANIMAL TOXICOLOGY

Hyperpigmentation of the thyroid has been produced by members of the tetracycline class in the following species: in rats by oxytetracycline, doxycycline, tetracycline PO4, and methacycline; in minipigs by doxycycline, minocycline, tetracycline PO4, and methacycline; in dogs by doxycycline and minocycline; in monkeys by minocycline.

Minocycline, tetracycline PO4, methacycline, doxycycline, tetracycline base, oxytetracycline HCl and tetracycline HCl were goitrogenic in rats fed a low iodine diet. This goitrogenic effect was accompanied by high radioactive iodine uptake.Administration of minocycline also produced a large goiter with high radioiodine uptake in rats fed a relatively high iodine diet.

Treatment of various animal species with this class of drugs has also resulted in the induction of thyroid hyperplasia in the following: in rats and dogs (minocycline), in chickens (chlortetracycline) and in rats and mice (oxytetracycline). Adrenal gland hyperplasia has been observed in goats and rats treated with oxytetracycline.

REFERENCES

1. Friedman JM and Polifka JE. Teratogenic Effects of Drugs. A Resource for Clinicians (TERIS).Baltimore, MD: The Johns Hopkins University Press: 2000: 149-195.
2. Cziezel AE and Rockenbauer M. Teratogenic study of doxycycline. Obstet Gynecol1997; 89:524-528.
3. Horne HW Jr. and Kundsin RB. The role of mycoplasma among 81 consecutive pregnancies: a prospective study. Int J Fertil1980; 25:315-317.
4. Hale T. Medications and Mothers Milk.9thedition. Amarillo, TX: Pharmasoft Publishing 2000; 225-226.

Rx only

Manufactured by:

Chartwell Pharmaceuticals, LLC.

Congers, NY 10920

Manufactured for:

Chartwell RX, LLC.

Congers, NY 10920

L70564

Rev: 03/2025

PRINCIPAL DISPLAY PANEL

NDC 62135-260-01

Doxycycline
Monohydrate
Capsules

50 mg
Rx Only
100 Capsules

PRINCIPAL DISPLAY PANEL

NDC 62135-261-01

Doxycycline
Monohydrate
Capsules

75 mg
Rx Only
100 Capsules

PRINCIPAL DISPLAY PANEL

NDC 62135-262-50

Doxycycline
Monohydrate
Capsules

100 mg
Rx Only
50 Capsules

PRINCIPAL DISPLAY PANEL

NDC 62135-262-60

Doxycycline
Monohydrate
Capsules

100 mg
Rx Only
60 Capsules

PRINCIPAL DISPLAY PANEL

NDC 62135-262-25

Doxycycline
Monohydrate
Capsules

100 mg
Rx Only
250 Capsules

PRINCIPAL DISPLAY PANEL

NDC 62135-263-60

Doxycycline
Monohydrate
Capsules

150 mg
Rx Only
60 Capsules